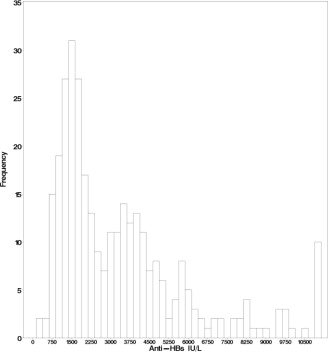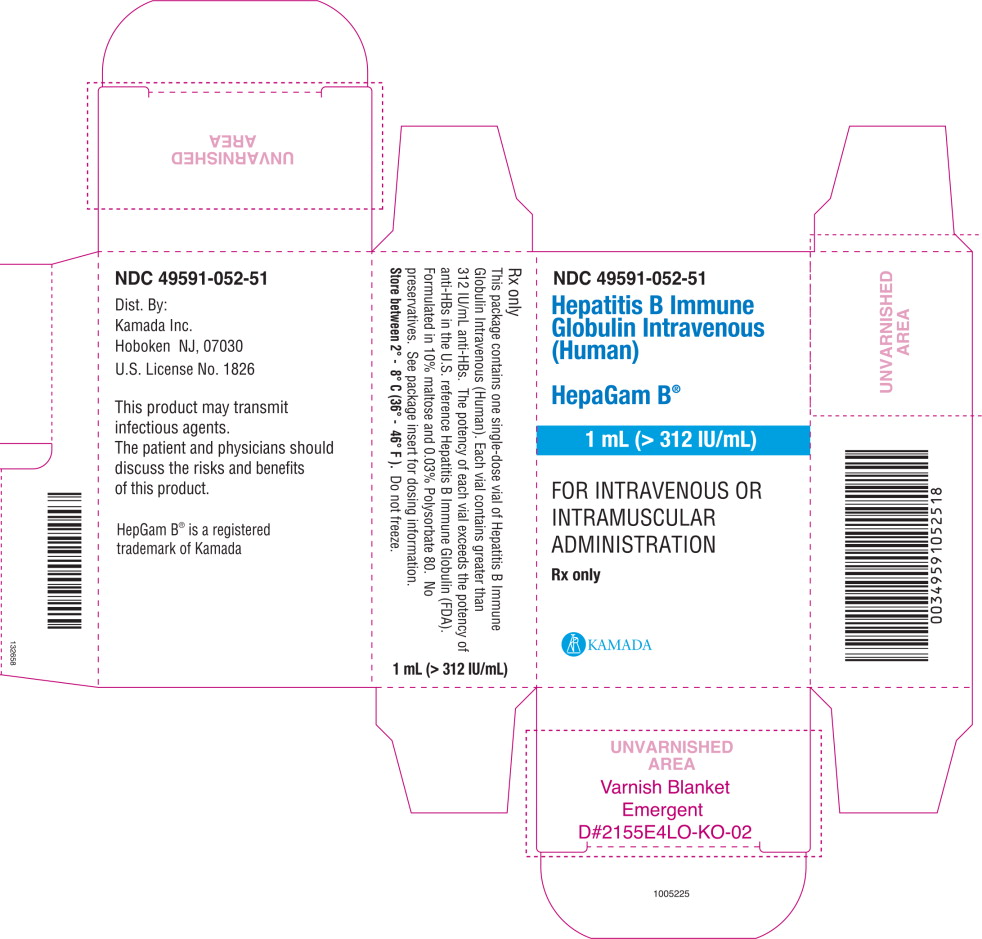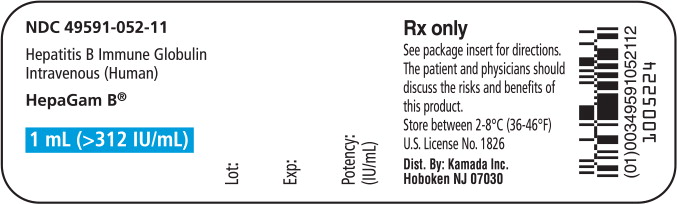 DRUG LABEL: HepaGam B
NDC: 49591-052 | Form: INJECTION, SOLUTION
Manufacturer: Kamada Ltd.
Category: other | Type: PLASMA DERIVATIVE
Date: 20231103

ACTIVE INGREDIENTS: HUMAN HEPATITIS B VIRUS IMMUNE GLOBULIN 312 [iU]/1 mL
INACTIVE INGREDIENTS: MALTOSE, UNSPECIFIED FORM; POLYSORBATE 80

HIGHLIGHTS OF PRESCRIBING INFORMATION

These highlights do not include all the information needed to use HepaGam B®safely and effectively. See full prescribing information for HepaGam B®.
HepaGam B®[Hepatitis B Immune Globulin Intravenous (Human)],
Sterile Solution for Intravenous or Intramuscular Injection Solvent/Detergent Treated and Filtered.> 312 IU per milliliter(Measured potency stamped on the vial label)
Initial U.S. Approval: 2006

1 INDICATIONS AND USAGE

- For Intravenous or Intramuscular Administration Only
- Prevention of Hepatitis B recurrence following Liver Transplantation in HBsAg-positive liver transplant patients (1.1).
- Postexposure Prophylaxis (1.2) in the following settings:
  - Acute Exposure to Blood Containing HBsAg
  - Perinatal Exposure of Infants Born to HBsAg-positive Mothers
  - Sexual Exposure to HBsAg-positive Persons
  - Household Exposure to Persons with Acute HBV Infection

2 DOSAGE AND ADMINISTRATION

Prevention of Hepatitis B recurrence following liver transplantation (2.1)

HepaGam B is administered intravenously at doses of 20,000 IU (calculated from the measured potency stamped on the vial label) according to the following regimen to attain serum anti-HBs > 500 IU per liter:

Anhepatic Phase | Week 1 Post-Operative | Weeks 2-12 Post-Operative | Month 4 onwards
First dose | Daily from Day 1-7 | Every two weeks from Day 14 | Monthly

Regularly monitor serum anti-HBs to allow for treatment adjustments.

Postexposure Prophylaxis (2.2)

HepaGam B must be administered intramuscularly only as directed below:

Acute Exposure to Blood Containing HBsAg | 0.06 milliliter per kilogram | Administer as soon as possible after exposure and within 24 hours if possible.
Perinatal Exposure of Infants Born to HBsAg-positive Mothers | 0.5 milliliter | Administer after physiologic stabilization of the infant and preferably within 12 hours of birth.
Sexual Exposure to HBsAg-positive Persons | 0.06 milliliter per kilogram | Administer HepaGam B within 14 days of the last sexual contact or if sexual contact with the infected person will continue.
Household Exposure to Persons with Acute HBV Infection | 0.5 milliliter | Infants < 12 months: Administer HepaGam B + Hepatitis B vaccine if primary caregiver has acute HBV infection.

3 DOSAGE FORMS AND STRENGTHS

1.0 milliliter sterile solution; single use vial (> 312 IU per milliliter). (3)

5.0 milliliters sterile solution; single use vial (> 312 IU per milliliter). (3)

The measured potency of each lot is stamped on the vial label.

4 CONTRAINDICATIONS

- History of anaphylactic or severe systemic reactions to human globulins (4)
- IgA deficient individuals may have the potential to develop IgA antibodies and have an anaphylactoid reaction. (4)
- IM injections may be contraindicated in patients with coagulation disorders. (4)

5 WARNINGS and PRECAUTIONS

- Hypersensitivity (5.1)
- Interference with Blood Glucose Testing (5.2)
- Monitoring: Serum Anti-HBs Antibody Levels (5.3)
- Infusion Reactions (5.4)
- Transmissible Infectious Agents (5.5)
- Coagulation Disorders (5.6)
- Thrombotic Events (5.7)

6 ADVERSE REACTIONS

The only adverse reactions observed in clinical trial subjects were hypotension and nausea (2% of clinical trial subjects). (6)

To report SUSPECTED ADVERSE REACTIONS, contact Kamada at 1-866-916-0077 or FDA at 1-800-FDA-1088 orwww.fda.gov/medwatch

7 DRUG INTERACTIONS

- Efficacy of live attenuated virus vaccines may be impaired by immune globulin administration; revaccination may be necessary. (7.1)
- Antibodies in HepaGam B may interfere with some serological tests. (7.2)
- Maltose in HepaGam B may interfere with non-glucose specific blood glucose testing systems. (7.3)

8 USE IN SPECIFIC POPULATIONS

- Pregnancy: No human or animal data. Use only if clearly needed. (8.1)
- Nursing mothers: Caution should be exercised (8.3)

FULL PRESCRIBING INFORMATION

1 INDICATIONS AND USAGE

HepaGam B [Hepatitis B immune globulin intravenous (Human)] is an intravenous immune globulin indicated for the following:

1.2 Post-exposure prophylaxis

including

- acute exposure to HBsAg-positive blood, plasma, or serum (parenteral exposure, direct mucus membrane contact, oral ingestion, etc.),
- perinatal exposure of infants born to HBsAg-positive mothers,
- sexual exposure to HBsAg-positive persons, and
- household exposure to persons with acute HBV infection.

2 DOSAGE AND ADMINISTRATION

2.1 Prevention of Hepatitis B recurrence following liver transplantation

Administer the first dose of HepaGam B during the grafting of the transplanted liver (the anhepatic phase) with subsequent dosing as recommended in Table 1.

Calculate the dosing from the measured potency of the particular lot of HepaGam B as stamped on the vial label.

Administer by intravenous infusion (Table 2).

Table 1 - HepaGam B Dosing Regimen for HBV-Related Liver Transplant Patients
Anhepatic Phase | Week 1 Post-Operative | Weeks 2-12 Post-Operative | Month 4 onwards
First dose | Daily from Day 1-7 | Every two weeks from Day 14 | Monthly
* Each dose should contain 20,000 IU calculated from the measured potency as stamped on the vial label [see Dosage Forms and Strengths (3) ].

Table 2 – HepaGam B Intravenous Infusion Rate
Route of Administration | Dosage | Infusion Rate
Intravenous | 20,000 IU per dose | 2 milliliters per minute. Decrease to 1 milliliter per minute or slower if the patient develops discomfort or infusion-related adverse reactions.

HepaGam B dose adjustments may be required in patients who fail to reach anti-HBs levels of 500 International Units per liter within the first week post-liver transplantation^1. Patients who have surgical bleeding or abdominal fluid drainage (> 500 milliliters) or patients who undergo plasmapheresis are particularly susceptible to extensive loss of circulated anti-HBs. In these cases, the dosing regimen should be increased to a half-dose (10,000 International Units calculated from the measured potency as stamped on the vial label) intravenously every 6 hours until the target anti-HBs is reached.

2.2 Postexposure Prophylaxis

Administer HepaGam B intramuscularly as recommended in Table 3.

Table 3 – HepaGam B Dosing Regimen for Postexposure Prophylaxis (Intramuscular)
Indication | Dosage | Instructions
Acute Exposure to Blood Containing HBsAg | 0.06 milliliter per kilogram | Administer HepaGam B as soon as possible after exposure. The value after seven days following exposure is unclear^(2, 3). For persons who refuse Hepatitis B vaccine or who are known non-responders to vaccine, give a second dose of HepaGam B one month after the first dose^2.
Perinatal exposure of Infants Born to HBsAg-positive mothers | 0.5 milliliter | Administer after physiologic stabilization of the infant and preferably within twelve hours of birth. Administer concurrently with Hepatitis B vaccine.
Sexual Exposure to HBsAg-Positive Persons | 0.06 milliliter per kilogram | Administer HepaGam B and Hepatitis B Vaccine series within 14 days of sexual contact or if sexual contact with the infected person will continue.
Household Exposure to Person with Acute HBV Infection | 0.5 milliliter | For infants less than twelve months of age administered concurrently with Hepatitis B Vaccine. Prophylaxis of other household contacts of persons with acute HBV infection is not indicated unless there is an identifiable blood exposure to the index patient, such as by sharing toothbrushes or razors. Treat such exposures like sexual exposures.

HepaGam B may be administered at the same time (but at a different site), or up to one month preceding Hepatitis B vaccination without impairing the active immune response to Hepatitis B vaccine^2,3.

2.3 Preparation

- Parenteral drug products should be inspected visually for particulate matter and discoloration prior to administration, whenever solution and container permit. Do not use if turbid.
- Do not shake vials during preparation to avoid foaming.
- The HepaGam B vial is for single use only. HepaGam B contains no preservatives.
- Promptly use any vial of HepaGam B that has been entered. Do not reuse or save for future use.
- For intravenous administration, administer HepaGam B through a separate intravenous line using an infusion pump.
- Use normal saline as the diluent if dilution of HepaGam B is preferred prior to intravenous administration. [ see Clinical Trials in Liver Transplant Patients (14.1) ]
- Do not use dextrose (5%) in water (D5W).
- Use a separate vial, sterile syringe, and needle for each individual patient, to prevent transmission of infectious agents from one person to another.

3 DOSAGE FORMS AND STRENGTHS

- HepaGam B is a sterile solution of purified gamma globulin (5% or 50 milligrams per milliliter) that contains greater than 312 International Units per milliliter of anti-HBs.
- The measured potency of each lot is stamped on the vial label.
- To ensure that the label claim of >312 International Units per milliliter is maintained over the product shelf life, a higher potency of 550 International Units per milliliter is targeted at the time of manufacture.
  - This higher target potency is a manufacturing requirement to account for variability in the potency assay and changes in potency over time.
  - The potency assay has a relative standard deviation (RSD) of approximately 10%.
  - The actual potency test result may vary from approximately 400 to 700 International Units per milliliter (3x RSD) based on statistical assessment of manufactured lots with a target potency of 550 International Units per milliliter.
- Calculate the dosing for the prevention of hepatitis B recurrence following liver transplantation from the measured potency of the particular lot of HepaGam B as stamped on the vial label.

4 CONTRAINDICATIONS

- Individuals known to have anaphylactic or severe systemic reactions to the parenteral administration of human globulin preparations should not receive HepaGam B.
- Individuals who are deficient in IgA may have the potential to develop anti-IgA antibodies and have an anaphylactoid reaction.
  - HepaGam B contains less than 40 micrograms per milliliter of IgA.
- For postexposure prophylaxis indications, HepaGam B must be administered intramuscularly only. In patients who have severe thrombocytopenia or any coagulation disorder that would contraindicate intramuscular injections, HepaGam B should be given only if the expected benefits outweigh the potential risks.

5 WARNINGS and PRECAUTIONS

5.1 Hypersensitivity

Severe hypersensitivity reactions may occur with HepaGam B. HepaGam B should be administered in a setting with appropriate equipment, medication and personnel trained in the management of hypersensitivity, anaphylaxis and shock. In case of hypersensitivity, discontinue HepaGam B infusion immediately and begin appropriate emergency treatment. Medications such as epinephrine and antihistamines should be available for immediate treatment of acute hypersensitivity reactions.

HepaGam B contains trace amounts of IgA (< 40 micrograms per milliliter). Patients with known antibodies to IgA may have a greater risk of severe hypersensitivity and anaphylactic reactions. HepaGam B is contraindicated in IgA deficient patients with antibodies against IgA and history of hypersensitivity reaction. (see CONTRAINDICATIONS[ 4])

5.2 Interference with Blood Glucose Testing

The maltose contained in HepaGam B can interfere with some types of blood glucose monitoring systems, i.e., those based on the glucose dehydrogenase pyrroloquinequinone (GDH-PQQ) method. This can result in falsely elevated glucose readings and, consequently, in the inappropriate administration of insulin, resulting in life-threatening hypoglycemia. Cases of true hypoglycemia may go untreated if the hypoglycemic state is masked by falsely elevated results.

5.3 Monitoring: Serum Anti-HBs Antibody Levels

Liver transplant patients should be monitored regularly for serum anti-HBs antibody levels using a quantitative assay to ensure that adequate protective levels are maintained.

5.4 Infusion Reactions

Certain adverse drug reactions may be related to the rate of infusion. The recommended infusion rate given under Dosage and Administration (2.1) must be closely followed. Patients must be closely monitored and carefully observed for any symptoms throughout the infusion period and immediately following an infusion.

5.5 Transmissible Infectious Agents

Because HepaGam B is made from human plasma, it may carry a risk of transmitting infectious agents, e.g. viruses, and, theoretically, the Creutzfeldt-Jakob disease (CJD) agent. No cases of transmission of viral diseases or CJD have been associated with the use of HepaGam B. All infections suspected by a physician possibly to have been transmitted by this product should be reported by the physician or other healthcare provider to Kamada at 1-866-916-0077.

5.6 Coagulation Disorders

For postexposure prophylaxis indications, HepaGam B must be administered intramuscularly only. In patients who have severe thrombocytopenia or any coagulation disorder that would contraindicate intramuscular injections, HepaGam B should be given only if the expected benefits outweigh the potential risks.

5.7 Thrombotic Events

Thrombotic events may occur during or following treatment with IGIV products^(4, 5). Patients at risk include those with a history of atherosclerosis, multiple cardiovascular risk factors, advanced age, impaired cardiac output, coagulation disorders, prolonged periods of immobilization, and/or known/suspected hyperviscosity.

Consider baseline assessment of blood viscosity in patients at risk for hyperviscosity including those with cryoglobulins, fasting chylomicronemia/markedly high triacylglycerols (triglycerides), or monoclonal gammopathies. For patients who are at risk of developing thrombotic events, administer HepaGam B at the minimum rate of infusion practicable.

6 ADVERSE REACTIONS

The only adverse reactions observed in clinical trial subjects were hypotension and nausea (2% of clinical trial subjects).

6.1 Clinical Trials Experience

Because clinical trials are conducted under widely varying conditions, adverse reaction rates observed in the clinical trials of a drug cannot be directly compared to rates in the clinical trials of another drug and may not reflect the rates observed in practice.

Hepatitis B-Related Liver Transplantation

In a clinical trial with 27 liver transplant patients, one adverse drug reaction was reported following the 578 (< 1%) HepaGam B infusions. This study utilized the recommended dosing regimen outlined in Table 1[ see Dosage and Administration (2.1) ]. The attributed adverse drug reaction of hypotension was reported in one patient. The reaction was associated with a single HepaGam B infusion during the first day post-transplant. The reaction resolved on the same day and did not recur with subsequent HepaGam B infusions.

Healthy Volunteer Studies

Seventy healthy male and female volunteers received a single dose of HepaGam B intramuscularly in clinical trials^6. Only one adverse drug reaction, an episode of nausea, was reported.

6.2 Postmarketing Experience

The following adverse reactions have been identified during postapproval use of HepaGam B. Because these reactions are reported voluntarily from a population of uncertain size, it is not always possible to reliably estimate their frequency or establish a causal relationship to drug exposure.

Postexposure Prophylaxis:

Dizziness has been reported in the postmarketing surveillance of HepaGam B for the postexposure prophylaxis indication.

Hepatitis B-Related Liver Transplantation:

The system organ classification of reported adverse reactions is provided below:

Cardiac disorders: | Sinus tachycardia
Gastrointestinal disorders: | Abdominal pain upper
Gastrointestinal disorders: | Nausea
General disorders and administration site conditions: | Chills
General disorders and administration site conditions: | Feeling cold
General disorders and administration site conditions: | Influenza like illness
General disorders and administration site conditions: | Pyrexia
Immune system disorders: | Anaphylactoid reaction
Immune system disorders: | Hypersensitivity
Investigations: | Lipase increased
Investigations: | Transaminases increased
Musculoskeletal and connective tissue disorders: | Back pain
Nervous system disorders: | Dizziness Headache
Respiratory, thoracic and mediastinal disorders: | Dyspnoea
Skin and subcutaneous tissue disorders: | Cold sweat

Healthcare professionals should report adverse reactions following the administration of HepaGam B to Kamada at 1-866-916-0077 or FDA's MedWatch reporting system at 1-800-FDA-1088 or www.fda.gov/medwatch.

7 DRUG INTERACTIONS

7.1 Live Attenuated Virus Vaccines

Immune globulin administration may impair the efficacy of live attenuated virus vaccines such as measles, rubella, mumps and varicella^2,3,7. Vaccination with live virus vaccines should be deferred until approximately three months after administration of HepaGam B, Hepatitis B Immune Globulin Intravenous (Human). Persons who received HepaGam B less than 14 days after live virus vaccination should be revaccinated 3 months after the administration of the immune globulin, unless serologic test results indicate that antibodies were produced^2,3.

There are no available data on drug interactions of HepaGam B with other medications.

7.2 Drug-Laboratory Interactions: Serological Testing

Antibodies present in HepaGam B may interfere with some serological tests. After administration of immune globulins like HepaGam B, a transitory increase of passively transferred antibodies in the patient's blood may result in misleading positive results in serological testing (e.g. Coombs' test).

7.3 Drug-Laboratory Interactions: Blood Glucose Testing

HepaGam B contains maltose which can interfere with certain types of blood glucose monitoring systems. [ See Warnings and Precautions (5.2).] Only testing systems that are glucose-specific should be used in patients receiving HepaGam B. This interference can result in falsely elevated glucose readings that can lead to untreated hypoglycemia or to inappropriate insulin administration, resulting in life-threatening hypoglycemia.

The product information of the blood glucose testing system, including that of the test strips, should be carefully reviewed to determine if the system is appropriate for use with maltose-containing parenteral products. If any uncertainty exists, contact the manufacturer of the testing system to determine if the system is appropriate for use with maltose-containing parenteral products.

8 USE IN SPECIFIC POPULATIONS

8.1 Pregnancy

Pregnancy Category C. Animal reproduction studies have not been conducted with HepaGam B. It is also not known whether HepaGam B can cause fetal harm when administered to a pregnant woman or can affect reproductive capacity. HepaGam B should be given to a pregnant woman only if clearly indicated.

8.3 Nursing Mothers

It is not known whether HepaGam B is excreted in human milk. Because many drugs are excreted in human milk, caution should be exercised when HepaGam B is administered to a nursing mother.

8.4 Pediatric Use

Safety and effectiveness have not been established in pediatric patients. However, for postexposure prophylaxis, the safety and effectiveness of similar hepatitis B immune globulins have been demonstrated in infants and children^8.

8.5 Geriatric Use

Clinical studies of HepaGam B did not include sufficient numbers of subjects aged 65 and over to determine whether they respond differently from younger subjects. Other reported clinical experience has not identified differences in responses between the elderly and younger patients. In general, dose selection for an elderly patient should be cautious, usually starting at the low end of the dosing range, reflecting the greater frequency of decreased hepatic, renal, or cardiac function, and of concomitant disease or other drug therapy.

10 OVERDOSAGE

Consequences of an overdose are not known. For intramuscular administration of HepaGam B, the only manifestations of overdose would be pain and tenderness at the injection site.

11 DESCRIPTION

HepaGam B, Hepatitis B Immune Globulin Intravenous (Human), is a solvent/detergent-treated sterile solution of purified gamma globulin containing anti-HBs. It is prepared from plasma donated by healthy, screened donors with high titers of anti-HBs that is purified by an anion-exchange column chromatography manufacturing method^9,10. HepaGam B is formulated as a 5% (50 milligrams per milliliter) protein solution with 10% maltose and 0.03% polysorbate 80 at pH 5.6. It is available in 1 milliliter and 5 milliliters single dose vials. The product appears as a clear to opalescent liquid. HepaGam B does not contain mercury. It contains no preservatives. This product is intended for single use. HepaGam B may be administered intravenously or intramuscularly dependent upon indication [see Dosage and Administration (2.)]. The source plasma used in the manufacture of this product was tested by FDA licensed Nucleic Acid testing (NAT) for HIV-1, HBV and HCV and found to be negative. Plasma also has been tested by in-process NAT for hepatitis A virus (HAV) and parvovirus B19 (B19) via minipool testing and the limit for B19 in the manufacturing pool is set not to exceed 10^4IU of B19 DNA per milliliter.

The manufacturing process contains two steps implemented specifically for virus clearance. The solvent and detergent step (using tri-n-butyl phosphate and Triton®X-100) is effective in the inactivation of enveloped viruses, such as hepatitis B, hepatitis C and HIV^11. Virus filtration, using a Planova®20N virus filter, is effective for the removal of viruses based on their size, including some non-enveloped viruses^12. These two viral clearance steps are designed to increase product safety by reducing the risk of transmission of enveloped and non-enveloped viruses. In addition to these two specific steps, the process step of anion-exchange chromatography was identified as contributing to the overall viral clearance capacity for small non-enveloped viruses.

The inactivation and reduction of known enveloped and non–enveloped model viruses were validated in laboratory studies as summarized in Table 4. The viruses employed for spiking studies were selected to represent those viruses that are potential contaminants in the product, and to represent a wide range of physiochemical properties in order to challenge the manufacturing process's ability for viral clearance in general.

Table 4 - Virus Reduction Values Obtained Through Validation Studies^8
 | Enveloped |  |  | Non-Enveloped
Genome | RNA |  | DNA | RNA |  | DNA
Virus | HIV-1 | BVDV | PRV | HAV | EMC | MMV | PPV
Family | retro | flavi | herpes | picorna |  | parvo
Size (nm) | 80-100 | 50-70 | 120-200 | 25-30 | 30 | 20-25 | 18-24
Anion Exchange Chromatography (partitioning) | Not evaluated |  |  | 2.3 | n.e. | 3.4 | n.e.
20N Filtration (size exclusion) | ≥ 4.7 | ≥ 3.5 | ≥ 5.6a | n.e. | 4.8 | n.e. | 4.1
Solvent/Detergent (inactivation) | ≥ 4.7 | ≥ 7.3 | ≥ 5.5 | Not evaluated
Total Reduction (log 10) | ≥ 9.4 | ≥ 10.8 | ≥ 11.1 | 2.3 | 4.8 | 3.4 | 4.1
Abbreviations:
HIV-1: human immunodeficiency virus-1; relevant virus for human immunodeficiency virus-1 and model for HIV-2
BVDV: bovine viral diarrhea virus; model virus for hepatitis C virus (HCV) and West Nile virus (WNV)
PRV: pseudorabies virus; model for large enveloped DNA viruses, including herpes
HAV: human hepatitis A virus; relevant virus for HAV and model for small non-enveloped viruses in general
EMC: encephalomyocarditis virus; model for HAV and for small non-enveloped viruses in general
MMV: murine minute virus; model for human parvovirus B19 and for small non-enveloped viruses in general
PPV: porcine parvovirus; model for human parvovirus B19 and for small non-enveloped viruses in general
n.e.: not evaluated
aThe PRV was retained by the 0.1 μm pre-filter during the virus validation. Since manufacturing employs a 0.1 μm pre-filter before the 20N filter, the claim of ≥ 5.6 reduction is considered applicable.

The product potency is expressed in international units (IU) by comparison to the World Health Organization (WHO) standard Hepatitis B Immune Globulin. Each vial contains greater than 312 IU per milliliter. The measured potency of each lot is stamped on the vial label [ see Dosage Forms and Strengths (3) ].

12 CLINICAL PHARMACOLOGY

12.1 Mechanism of Action

HepaGam B provides passive immunization for individuals exposed to the hepatitis B virus, by binding to the surface antigen and reducing the rate of hepatitis B infection^13-16.

12.2 Pharmacokinetics

The pharmacokinetic profile of HepaGam B has been evaluated in two 84-day clinical trials in which 70 healthy subjects received an intramuscular injection of 0.06 milliliter per kilogram of HepaGam B. The mean peak concentrations (Cmax) in both studies were comparable and occurred within 4-5 days of administration. Both studies demonstrated mean elimination half-lives (t½) following IM administration of 22 to 25 days. The mean clearance rate was 0.21 to 0.24 liter per day and the volume of distribution was approximately 7.5 liter. Thus, HepaGam B demonstrates pharmacokinetic parameters similar to those reported by Scheiermann and Kuwert^17.

The maximum concentration of anti-HBs achieved by HepaGam B was consistent with that of two other licensed comparator Hepatitis B Immune Globulin (Human) products^6. Comparability of pharmacokinetics between HepaGam B and a commercially available hepatitis B immune globulin product administered IM indicates that comparable efficacy of HepaGam B should be inferred.

14 CLINICAL STUDIES

14.1 Clinical Trials in Liver Transplant Patients

A clinical trial examined the effectiveness of HepaGam B in the prevention of hepatitis B recurrence following liver transplantation. The study was a multi-center, open-labeled, superiority study involving HBsAg-positive/HBeAg-negative liver transplant patients. The study included two arms, an active treatment group of patients enrolled to receive the described dosing regimen of HepaGam B starting during transplant and continuing over the course of a year, and a retrospective untreated control group of historical patients with data gathered by chart review.

There were 27 liver transplant patients who received HepaGam B and 14 retrospective untreated control patients. The patients in both groups were HBsAg-positive/HBeAg-negative liver transplant patients who met similar entry criteria, had similar medical history and had similar status at transplant based on MELD and/or ChildPugh-Turcotte scores.

In the active treatment group, HepaGam B intravenous doses of 35 milliliters were initiated during transplant according to the regimen identified in Table 1[see Dosage and Administration (2.1) ]. As a result of the targeted potency of 550 IU per milliliter at the time of manufacture [ see Dosage Forms and Strengths (3.) ], the 35 milliliter doses of HepaGam B used in this study actually contained between 17,000 and 23,000 IU anti-HBs. These 35 milliliter doses consistently yielded anti-HBs trough levels > 500 IU per liter (99% of all anti-HBs levels were > 500 IU per liter; see Figure 1). Patients received HepaGam B doses diluted with 50 mL of saline.

Figure 1: Frequency Histogram of Trough anti-HBs Levels more than 30 days after Transplant

Values below the target trough were only observed in the 2 patients with HBV recurrence who had anti-HBs levels < 150 IU per liter at the time of seroconversion.

For the efficacy endpoint of the proportion of patients with HBV recurrence (HBsAg positive and/or HBeAg positive after 4 weeks post-OLT), a significant treatment effect was observed. As summarized in Table 5, HBV recurrence was seen in 2/24 or 8.3% of HepaGam B patients compared to 12/14 or 86% of retrospective untreated control patients (see Table 5). Two of the HepaGam B patients who died within 28 days post-transplant were excluded from all efficacy analyses, but included for safety analyses. The deaths were not HBV or study drug related.

Table 5 - Results of Study HB-005 for the Prevention of Hepatitis B Recurrence Following Liver Transplantation
 | HepaGam B | Retrospective Untreated Control | P-value (Fisher's Exact Test)
HBV RecurrenceProportion, % (95% confidence interval) | 8.3 (0.1 -27.0) | 85.7 (57.2 -98.2) | < 0.001

The conclusion that HepaGam B monotherapy post-OLT is effective at preventing HBV recurrence post-OLT is further supported by the secondary endpoints of time to recurrence, survival, anti-HBs levels, biochemical markers of liver inflammation, and liver biopsy. Time to recurrence for the HepaGam B treatment group was 358 days for two HBV recurrent patients. In comparison, the retrospective untreated control patients had a median time to recurrence of 88 days with a 95% confidence interval of 47 to 125 days. Survival calculations showed that 96% (23/24) of patients in the active treatment group survived for at least 1 year post-OLT compared to 43% (6/14) retrospective control patients. The endpoints for HBV recurrence were supported by an observed drop in anti-HBs levels, elevated liver function tests, and abnormal liver biopsy result at the time of recurrence.

HepaGam B is recommended in patients who have no or low levels of viral replication at the time of liver transplantation. The clinical trial evaluating HepaGam B in liver transplant patients selected patients with no or low replication status only. HepaGam B therapy has not been evaluated in combination with antiviral therapy post-transplantation.

15 REFERENCES

1. McGory RW, Ishitani MB, Oliveira WM, Stevenson WC, McCullough CS, Dickson RC et al. Improved outcome of orthotopic liver transplantation for chronic hepatitis B cirrhosis with aggressive passive immunization. Transplantation 1996; 61(9):1358-1364.
2. CDC. A comprehensive immunization strategy to eliminate transmission of hepatitis B virus infection in the United States. Recommendations of the Advisory Committee on Immunization Practices (ACIP). Part 1: Immunization of infants, children, and adolescents. MMWR 2005; 54(RR-16): 1-32.
3. CDC. A comprehensive immunization strategy to eliminate transmission of hepatitis B virus infection in the United States. Recommendations of the Advisory Committee on Immunization Practices (ACIP). Part 2: Immunization of adults. MMWR 2006; 55(RR-16): 1-33.
4. Dalakas MC. High-dose intravenous immunoglobulin and serum viscosity: risk of precipitating thromboembolic events. Neurology 1994; 44:223-226.
5. Woodruff RK, et al.: Fatal thrombotic events during treatment of autoimmune thrombocytopenia with intravenous immunoglobulin in elderly patients. Lancet 1986; 2:217-218.
6. Unpublished data on file.
7. Committee for Proprietary Medicinal Products (CPMP). Core SPC for human plasma derived hepatitis-B immunoglobulin for intravenous use (CPMP/BPWG/4027/02). London, UK: The European Agency for the Evaluation of Medicinal Products. 2003.
8. CDC: Recommendations for protection against viral hepatitis. Recommendations of the Immunization Practices Advisory Committee (ACIP). MMWR 1985; 34(22):313-335.
9. Bowman JM, et al. WinRho: Rh immune globulin prepared by ion exchange for intravenous use. Canadian Med Assoc J 1980; 123:1121-5.
10. Friesen AD, et al. Column ion-exchange preparation and characterization of an Rh immune globulin (WinRho) for intravenous use. Journal Appl Biochem 1981; 3:164-75.
11. Horowitz B. Investigations into the application of tri(n-butyl)phosphate /detergent mixtures to blood derivatives. Morgenthaler J (ed): Virus Inactivation in Plasma Products, Curr Stud Hematol Blood Transfus 1989; 56:83-96.
12. Burnouf T. Value of virus filtration as method for improving the safety of plasma products. Vox Sang 1996; 70:235-6.
13. Grady GF, Lee VA. Hepatitis B immune globulin - prevention of hepatitis from accidental exposure among medical personnel. N Engl J Med 1975; 293:1067-70.
14. Seeff LB, et al. Type B hepatitis after needle-stick exposure: Prevention with hepatitis B immune globulin. Ann Int Med 1978; 88: 285-93.
15. Krugman S, Giles JP. Viral hepatitis, type B (MS-2-strain). Further observations on natural history and prevention. N Engl J Med 1973; 288: 755-60.
16. Hoofnagle JH, et al. Passive-active immunity from hepatitis B immune globulin. Ann Int Med 1979; 91:813-8.
17. Scheiermann N, Kuwert EK. Uptake and elimination of hepatitis B immunoglobulins after intramuscular application in man. Dev Biol Standard 1983; 54:347-55.

16 HOW SUPPLIED/STORAGE AND HANDLING

NDC 49591-052-51; a carton containing a 1.0 milliliter single dose vial (> 312 IU per milliliter; measured potency of each lot is stamped on the vial label) and a package insert.

NDC 49591-051-51; a carton containing a 5.0 milliliter single dose vial (> 312 IU per milliliter; measure potency of each lot is stamped on the vial label) and a package insert.

Store at 36 to 46 °F (2 to 8 °C). Do not freeze. Do not use after expiration date. Use within 6 hours after the vial has been entered.

17 PATIENT COUNSELING INFORMATION

- Inform patients of the following:
  - HepaGam B is prepared from human plasma, and therefore, may contain infectious agents such as viruses that can cause disease.
  - The risk that such products will transmit an infectious agent has been reduced by screening plasma donors for prior exposure to certain viruses, by testing for the presence of certain current virus infections, and by inactivating and/or removing certain viruses during manufacturing.
  - Despite these measures, such products can still potentially transmit disease.
  - There is also the possibility that unknown infectious agents may be present in such products.
- Tell patients that persons known to have severe, potentially life-threatening reactions to human globulin products should not receive HepaGam B or any other immune globulin products unless the risk has been justified.
- Tell patients that persons who are deficient in IgA may have the potential for developing anti-IgA antibodies and have severe potentially life threatening allergic reactions.
  - In case of allergic or anaphylactic reaction, the infusion should be stopped immediately.
  - In case of shock, the current medical standards for treatment of shock should be observed.
- Advise Liver Transplant patients about the potential interference with non-glucose specific monitoring systems.
  - The maltose contained in HepaGam B can interfere with some types of blood glucose monitoring systems.
  - Only testing systems that are glucose-specific should be used in patients receiving HepaGam B.
  - This inference can result in falsely elevated glucose readings that can lead to untreated hypoglycemia or to inappropriate insulin administration, resulting in life-threatening hypoglycemia.

HepaGam B®[Hepatitis B Immune Globulin Intravenous (Human)] Sterile Solution for Injection and any and all Kamada brand, product, service and feature names, logos, slogans are trademarks or registered trademarks of Kamada. All rights reserved.

PLANOVA®is a registered trademark of Asahi Kasei Medical Co., Ltd, TRITON®is a registered trademark of Union Carbide Corporation.

Distributed by:
Kamada Inc.
Hoboken, NJ 07030
U.S. License No. 1826

Principal Display Panel – 1 mL Carton Label

NDC 49591-052-51

Hepatitis B Immune
Globulin Intravenous
(Human)

HepaGam B®

1 mL (> 312 lU/mL)

FOR INTRAVENOUS OR
INTRAMUSCULAR
ADMINISTRATION

Rx only

KAMADA

Principal Display Panel – 1 mL Vial Label

NDC 49591-052-11

Hepatitis B Immune Globulin
Intravenous (Human)

HepaGam B®

1 mL (> 312 lU/mL)